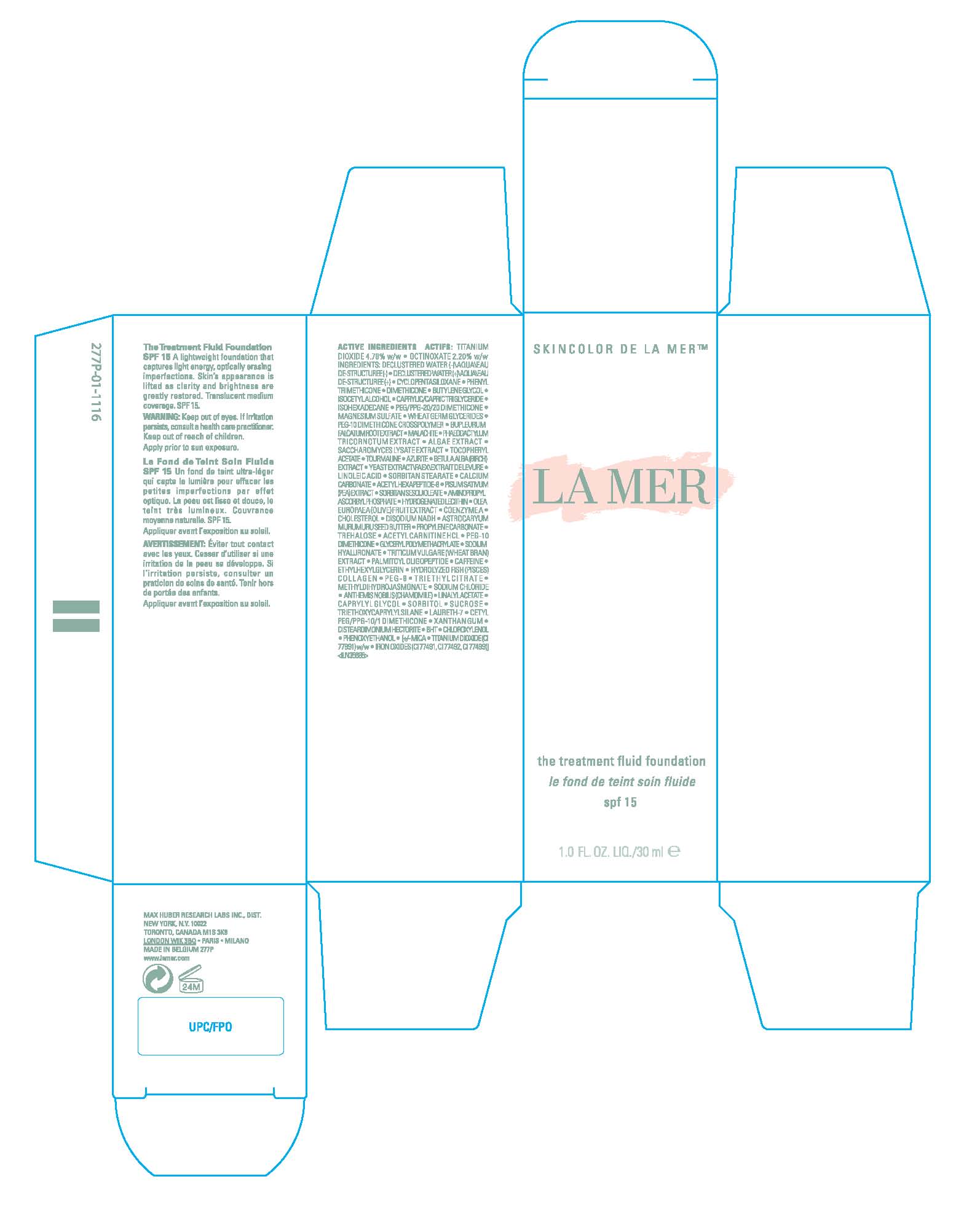 DRUG LABEL: LA MER THE TREATMENT FLUID FOUNDATION
NDC: 65966-001 | Form: LIQUID
Manufacturer: MAX HUBER RESEARCH LAB INC
Category: otc | Type: HUMAN OTC DRUG LABEL
Date: 20100402

ACTIVE INGREDIENTS: TITANIUM DIOXIDE 4.7 mL/100 mL; OCTINOXATE 2.2 mL/100 mL

ACTIVE INGREDIENT

ACTIVE INGREDIENTS: TITANIUM DIOXIDE 4.7%, OCTINOXATE 2.2%

WARNINGS

WARNING: KEEP OUT OF EYES. IF IRRITATION PERSISTS, CONSULT A HEALTH CARE PRACTITIONER. KEEP OUT OF REACH OF CHILDREN.

WHEN USING

DIRECTIONS: APPLY PRIOR TO SUN EXPOSURE

PACKAGE LABEL

PRINCIPAL DISPLAY PANEL

LA MER

THE TREATMENT FLUID FOUNDATION

SPF 15

1.0 FL OZ/30 mL

MAX HUBER RESEARCH LAB INC.

NEW YORK, NY 10022